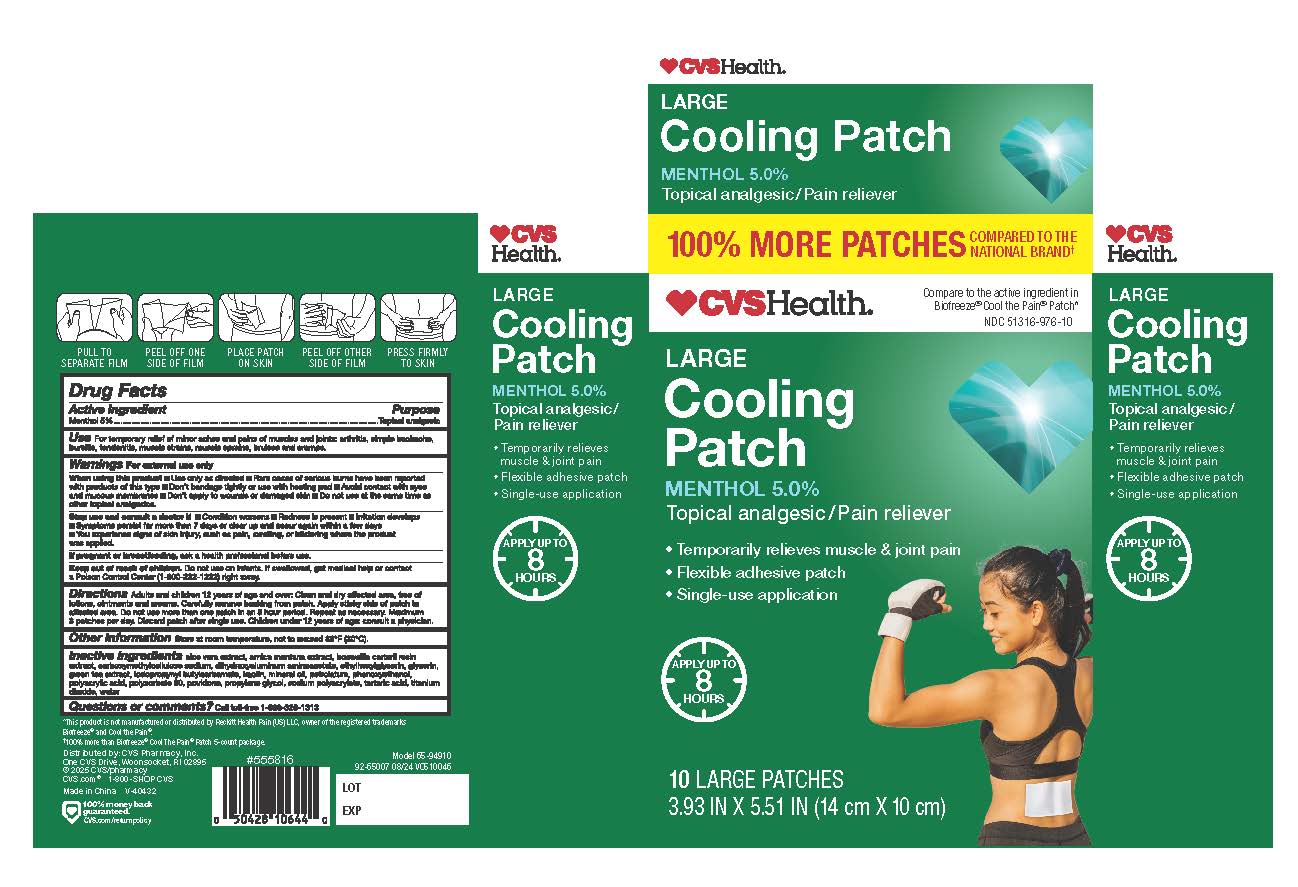 DRUG LABEL: CVS Health Cooling Patch
NDC: 51316-976 | Form: PATCH
Manufacturer: CVS Pharmacy, Inc
Category: otc | Type: HUMAN OTC DRUG LABEL
Date: 20251228

ACTIVE INGREDIENTS: MENTHOL 5 g/100 g
INACTIVE INGREDIENTS: GLYCERIN; DIHYDROXYALUMINUM AMINOACETATE; CARBOXYMETHYLCELLULOSE SODIUM, UNSPECIFIED FORM; WATER; PHENOXYETHANOL; KAOLIN; ALOE VERA LEAF; MINERAL OIL; PETROLATUM; IODOPROPYNYL BUTYLCARBAMATE; FRANKINCENSE; POLYACRYLIC ACID (450000 MW); GREEN TEA LEAF; ETHYLHEXYLGLYCERIN; POLYSORBATE 80; ARNICA MONTANA FLOWER; TARTARIC ACID; POVIDONE; PROPYLENE GLYCOL; SODIUM POLYACRYLATE (2500000 MW); TITANIUM DIOXIDE

CVS Health Cooling Patch

Active Ingredient

Menthol 5%

Purpose

Topical analgesic

Uses

For temporary relief of minor aches and pains of muscles and joints: arthritis, simple backache, bursitis, tendonitis, muscle strains, bruises and cramps

Warnings

For external use only

When using this product

■Use only as directed ■ Rare cases of serious burns have been reported with products of this type ■Don't bandage tightly or use with heating pad ■ Avoid contact with eyes and mucous membranes ■Don't apply to wounds or damaged skin ■ Do not use at the same time as other topical analgesics.

Stop use and consult a doctor if

- condition worsens
- redness is present
- irritation develops
- symptoms persist for more than 7 days or clear up and occur again within a few days
- you experience signs of skin injury, such as pain, swelling, or blistering where the product was applied

If pregnant or breastfeeding

ask a health professional before use.

Keep out of reach of children

Do not use on infants. If swallowed, get medical help or contact a Poison Control Center (1-800-222-1222) right away.

Directions

Adults and children 12 years of age and over: Clean and dry affected area, free of lotions, ointments and creams. Carefully remove backing from patch. Apply sticky side of patch to affected area. Do not use more than one patch up to 8 hours period. Repeat as necessary. Maximum 3 patches per day. Discard patch after single use. Children under 12 years of age: consult a physician.

Other information

Store at room temperature, not to exceed 86ºF (30°C).

Inactive Ingredients

aloe vera extract, arnica montana extract, boswellia carterii resin extract, carboxymethylcellulose sodium, dihydroxyaluminum aminoacetate, ethylhexylglycerin, glycerin, green tea extract, iodopropynyl butylcarbamate, kaolin, mineral oil, petrolatum, phenoxyethanol, polyacrylic acid, polysorbate 80, povidone, propylene glycol, sodium polyacrylate, tartaric acid, titanium dioxide, water

Questions or comments

Call toll free 1-866-326-1313